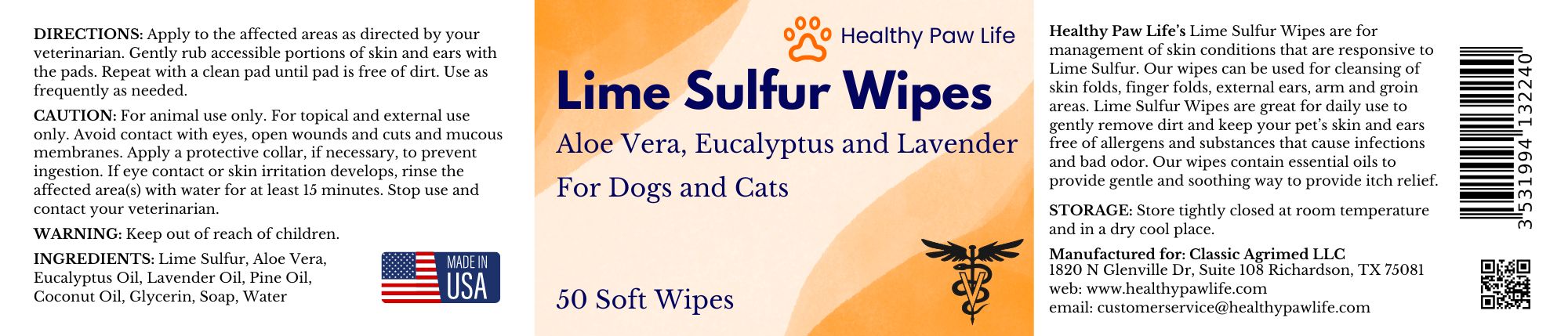 DRUG LABEL: HEALTHY PAW LIFE LIME SULFUR WIPES
NDC: 86130-905 | Form: LIQUID
Manufacturer: CLASSIC AGRIMED LLC
Category: animal | Type: OTC ANIMAL DRUG LABEL
Date: 20240502

ACTIVE INGREDIENTS: CALCIUM POLYSULFIDE 1 g/100 g

HEALTHY PAW LIFE'S LIME SULFUR WIPES

Healthy Paw Life’s Lime Sulfur Wipes are for management of skin conditions that are responsive to Lime Sulfur. Our wipes can be used for cleansing of skin folds, finger folds, external ears, arm and groin areas. Lime Sulfur Wipes are great for daily use to gently remove dirt and keep your pet’s skin and ears free of allergens and substances that cause infections and bad odor. Our wipes contain essential oils to provide gentle and soothing way to provide itch relief.

DIRECTIONS: Apply to the affected areas as directed by your veterinarian. Gently rub accessible portions of skin and ears with the pads. Repeat with a clean pad until pad is free of dirt. Use as frequently as needed.

CAUTION: For animal use only. For topical and external use only. Avoid contact with eyes, open wounds and cuts and mucous membranes. Apply a protective collar, if necessary, to prevent ingestion. If eye contact or skin irritation develops, rinse the affected area(s) with water for at least 15 minutes. Stop use and contact your veterinarian.

WARNING: Keep out of reach of children.

STORAGE: Store tightly closed at room temperature and in a dry cool place.

Manufactured for: Classic Agrimed LLC

1820 N Glenville Dr, Suite 108 Richardson, TX 75081
web: www.healthypawlife.com
email: customerservice@healthypawlife.com